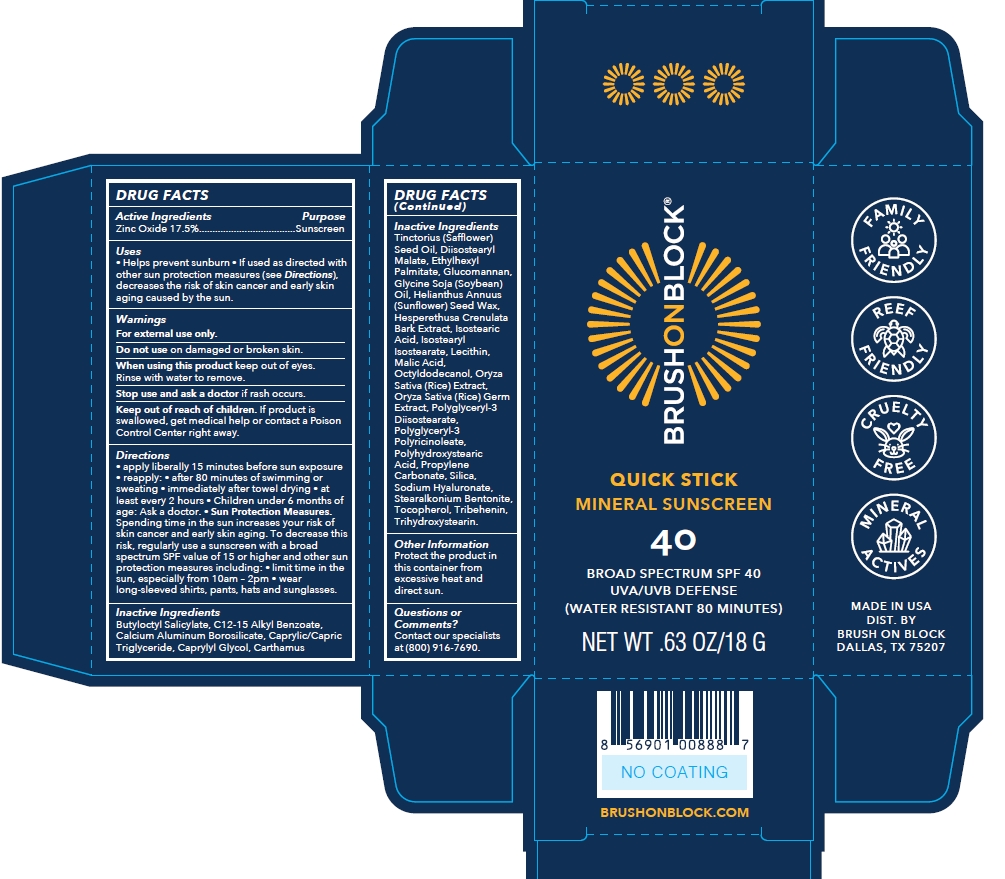 DRUG LABEL: Brush On Block Quick Stick SPF 40 Mineral Stick
NDC: 58274-012 | Form: STICK
Manufacturer: SPF Ventures LLC
Category: otc | Type: HUMAN OTC DRUG LABEL
Date: 20240304

ACTIVE INGREDIENTS: ZINC OXIDE 17.5 g/100 g
INACTIVE INGREDIENTS: HYALURONATE SODIUM; TRIHYDROXYSTEARIN; ISOSTEARYL ISOSTEARATE; RICE GERM; ALKYL (C12-15) BENZOATE; POLYHYDROXYSTEARIC ACID (2300 MW); SOYBEAN OIL; MALIC ACID; POLYGLYCERYL-3 PENTARICINOLEATE; PROPYLENE CARBONATE; TOCOPHEROL; OCTYLDODECANOL; HELIANTHUS ANNUUS SEED WAX; SAFFLOWER OIL; CALCIUM ALUMINUM BOROSILICATE; CAPRYLYL GLYCOL; NARINGI CRENULATA WHOLE; MEDIUM-CHAIN TRIGLYCERIDES; DIISOSTEARYL MALATE; SILICON DIOXIDE; ETHYLHEXYL PALMITATE; KONJAC MANNAN; TRIBEHENIN; BUTYLOCTYL SALICYLATE; ISOSTEARIC ACID; POLYGLYCERYL-3 DIISOSTEARATE; LECITHIN, SUNFLOWER; STEARALKONIUM HECTORITE

Brush On Block Quick Stick SPF 40 Mineral Stick

Active ingredient

Zinc Oxide 17.5%

Purpose

Sunscreen

Uses

- Helps prevent sunburn
- If used as directed with other sun protection measures (see Directions), decreases the risk of skin cancer and early skin aging caused by the sun.

Warnings

For external use only

Do not use on damaged or broken skin

When using this product keep out of eyes. Rinse with water to remove.

Stop use and ask a doctor if rash occurs.

Keep out of reach of children

If product is swallowed, get medical help or contact a Poison Control Center right away.

Directions

- apply liberally 15 minutes before sun exposure.
- reapply at least every 2 hours
- use a water resistant sunscreen if swimming or sweating
- Children under 6 months of age: Ask a doctor.
- Sunprotection Measures. Spending time in the sun increases your risk of skin cancer and early skin aging. To decrease this risk, regularly use a sunscreen with a broad spectrum SPF value of 15 or higher and other sun protection measures including:
- limit time in the sun, especially from 10am-2pm
- wear long-sleeved shirts, pants, hats and sunglasses.

Inactive Ingredients

C12-15 ALKYL BENZOATE

CAPRYLIC/CAPRIC TRIGLYCERIDE

HELIANTHUS ANNUUS (SUNFLOWER) SEED WAX

ISOSTEARYL ISOSTEARATE

BUTYLOCTYL SALICYLATE

TRIBEHENIN

DIISOSTEARYL MALATE

SILICA

OCTYLDODECANOL

CARTHAMUS TINCTORIUS (SAFFLOWER) SEED OIL

POLYHYDROXYSTEARIC ACID

STEARALKONIUM BENTONITE

CALCIUM ALUMINUM BOROSILICATE

CAPRYLYL GLYCOL

ETHYLHEXYL PALMITATE

GLUCOMANNAN

GLYCINE SOJA (SOYBEAN) OIL

HESPERETHUSA CRENULATA BARK EXTRACT

ISOSTEARIC ACID

LECITHIN

MALIC ACID

ORYZA SATIVA (RICE) EXTRACT

ORYZA SATIVA (RICE) GERM EXTRACT

POLYGLYCERYL-3 DIISOSTEARATE

POLYGLYCERYL-3 POLYRICINOLEATE

PROPYLENE CARBONATE

SODIUM HYALURONATE

TOCOPHEROL

TRIHYDROXYSTEARIN

Other Information

Protect the product in this container from excessive heat and direct sun